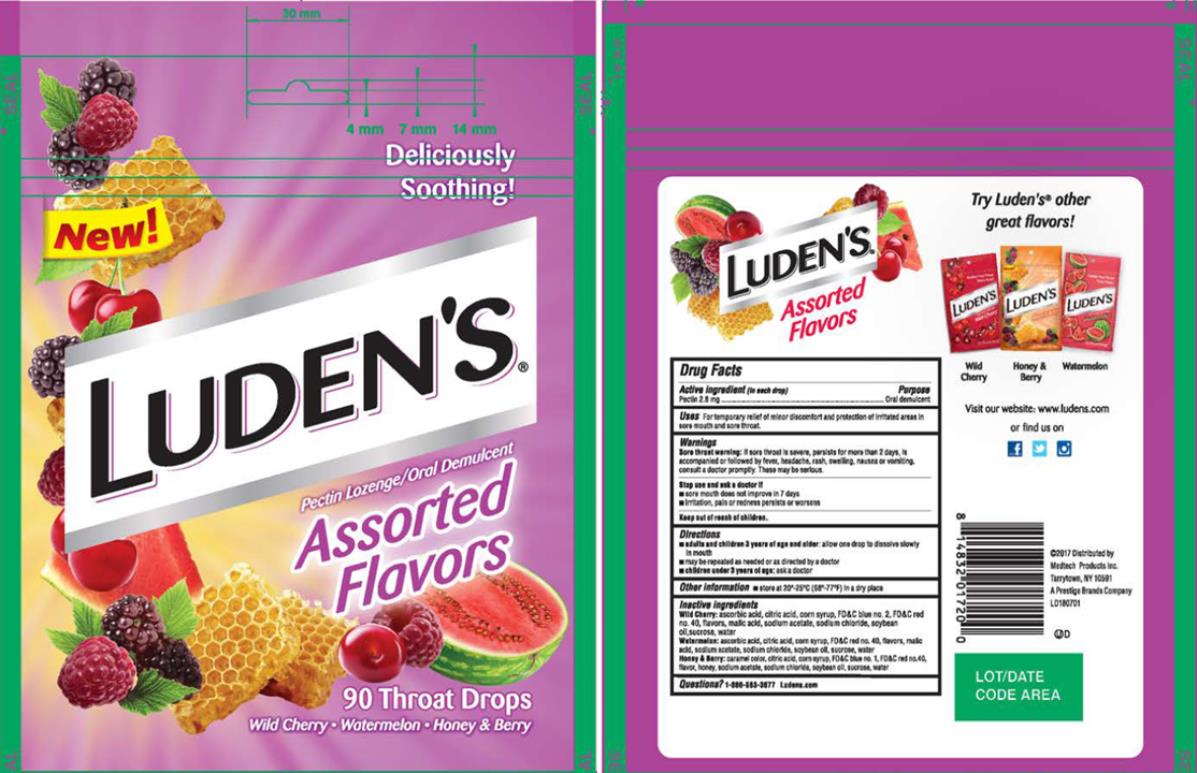 DRUG LABEL: Ludens Assorted Flavors
NDC: 52183-217 | Form: LOZENGE
Manufacturer: Prestige Brands Holdings, Inc.
Category: otc | Type: HUMAN OTC DRUG LABEL
Date: 20241025

ACTIVE INGREDIENTS: PECTIN 2.8 mg/1 1
INACTIVE INGREDIENTS: ASCORBIC ACID; CITRIC ACID MONOHYDRATE; CORN SYRUP; FD&C BLUE NO. 2; FD&C RED NO. 40; MALIC ACID; SODIUM ACETATE; SODIUM CHLORIDE; SOYBEAN OIL; SUCROSE; WATER; CARAMEL; FD&C BLUE NO. 1; HONEY

Ludens Assorted Flavors

Drug Facts

Active ingredient (in each drop)

Pectin 2.8 mg

Purpose

Oral demulcent

Uses

For temporary relief of minor discomfort and protection of irritated areas in sore mouth and sore throat.

Warnings

Sore throat warning: if sore throat is severe, persists for more than 2 days, is accompanied or followed by fever, headache, rash, swelling, nausea, or vomiting, consult a doctor promptly. These may be serious.

Stop use and ask a doctor if

• sore mouth does not improve in 7 days

• irritation, pain or redness persists or worsens

Directions

• adults and children 3 years of age and older: allow one drop to dissolve slowly in mouth.

• may be repeated as needed or as directed by a doctor

• children under 3 years of age: ask a doctor

Other information

store at 20°-25°C (68°-77°F) in a dry place

Inactive ingredients

Wild Cherry: ascorbic acid, citric acid, corn syrup, FD&C blue no. 2, FD&C red no. 40, flavors, malic acid, sodium acetate, sodium chloride, soybean oil, sucrose, water

Watermelon: ascorbic acid, citric acid, corn syrup, FD&C red no. 40, flavors, malic acid, sodium acetate, sodium chloride, soybean oil, sucrose, water

Honey & Berry: caramel color, citric acid, corn syrup, FD&C blue no. 1, FD&C red no. 40, flavor, honey, sodium acetate, sodium chloride, soybean oil, sucrose, water

Questions?

1-866-583-3677 Ludens.com

PRINCIPAL DISPLAY PANEL

Luden’s
Pectin Lozenge/ Oral Demulcent
Assorted flavors
Wild Cherry • Watermelon • Honey & Berry
90 Throat Drops